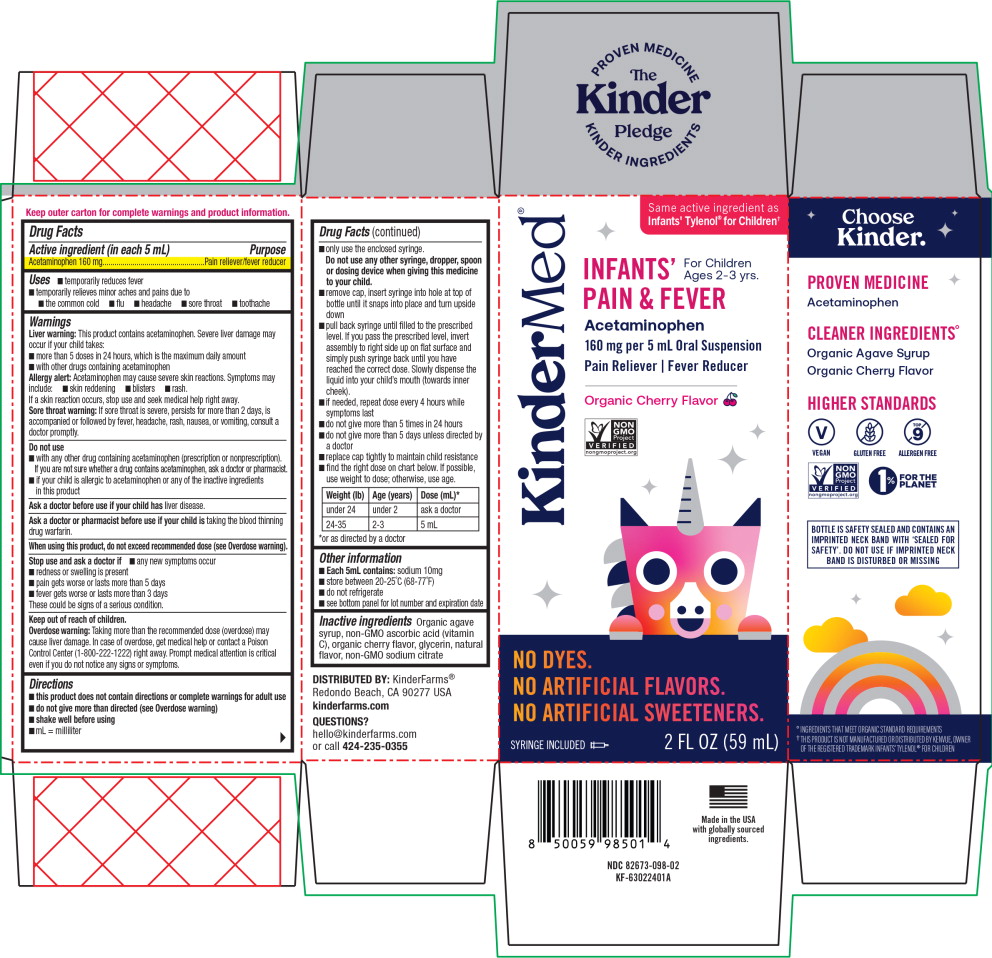 DRUG LABEL: Infants Pain and Fever
NDC: 82673-098 | Form: SUSPENSION
Manufacturer: KinderFarms, LLC
Category: otc | Type: HUMAN OTC DRUG LABEL
Date: 20250529

ACTIVE INGREDIENTS: ACETAMINOPHEN 160 mg/5 mL
INACTIVE INGREDIENTS: AGAVE TEQUILANA JUICE; ASCORBIC ACID; GLYCERIN; SODIUM CITRATE, UNSPECIFIED FORM

Drug Facts

Active ingredient (in each 5 mL)

Acetaminophen 160 mg

Purpose

Pain reliever/fever reducer

Uses

- temporarily reduces fever
- temporarily relieves minor aches and pains due to
  - the common cold
  - flu
  - headache
  - sore throat
  - toothache

Warnings

Liver warning: This product contains acetaminophen. Severe liver damage may occur if your child takes:

- more than 5 doses in 24 hours, which is the maximum daily amount
- with other drugs containing acetaminophen

Allergy alert: Acetaminophen may cause severe skin reactions. Symptoms may include:

- skin reddening
- blisters
- rash.

If a skin reaction occurs, stop use and seek medical help right away.

Sore throat warning: If sore throat is severe, persists for more than 2 days, is accompanied or followed by fever, headache, rash, nausea, or vomiting, consult a doctor promptly.

Do not use

- with any other drug containing acetaminophen (prescription or nonprescription). If you are not sure whether a drug contains acetaminophen, ask a doctor or pharmacist.
- if your child is allergic to acetaminophen or any of the inactive ingredients in this product

Ask a doctor before use if your child has liver disease.

Ask a doctor or pharmacist before use if your child is taking the blood thinning drug warfarin.

When using this product, do not exceed recommended dose (see Overdose warning).

Stop use and ask a doctor if

- any new symptoms occur
- redness or swelling is present
- pain gets worse or lasts more than 5 days
- fever gets worse or lasts more than 3 days

These could be signs of a serious condition.

Overdose warning:

Taking more than the recommended dose (overdose) may cause liver damage. In case of overdose, get medical help or contact a Poison Control Center (1-800-222-1222) right away. Prompt medical attention is critical even if you do not notice any signs or symptoms.

Directions

- this product does not contain directions or complete warnings for adult use
- do not give more than directed (see Overdose warning)
- shake well before using
- mL = milliliter
- only use the enclosed syringe.
  Do not use any other syringe, dropper, spoon or dosing device when giving this medicine to your child.
- remove cap, insert syringe into hole at top of bottle until it snaps into place and turn upside down
- pull back syringe until filled to the prescribed level. If you pass the prescribed level, invert assembly to right side up on flat surface and simply push syringe back until you have reached the correct dose. Slowly dispense the liquid into your child's mouth (towards inner cheek).
- if needed, repeat dose every 4 hours while symptoms last
- do not give more than 5 times in 24 hours
- do not give more than 5 days unless directed by a doctor
- replace cap tightly to maintain child resistance
- find the right dose on chart below. If possible, use weight to dose; otherwise, use age.

Weight (lb) | Age (years) | Dose (mL)*
under 24 | under 2 | ask a doctor
24-35 | 2-3 | 5 mL
*or as directed by a doctor

Other information

- Each 5mL contains: sodium 10mg
- store between 20-25˚C (68-77˚F)
- do not refrigerate
- see bottom panel for lot number and expiration date

Inactive ingredients

Organic agave syrup, non-GMO ascorbic acid (vitamin C), organic cherry flavor, glycerin, natural flavor, non-GMO sodium citrate

DISTRIBUTED BY: KinderFarms®
Redondo Beach, CA 90277 USA
kinderfarms.com

QUESTIONS?

hello@kinderfarms.com
or call 424-235-0355

Principal Display Panel - 59 mL Carton Label

KinderMed®

Same active ingredient as
Infants' Tylenol® for Children†

For Children
Ages 2-3 yrs.

INFANTS'
PAIN & FEVER
Acetaminophen

160 mg per 5 mL Oral Suspension

Pain Reliever | Fever Reducer

Organic Cherry Flavor

NON
GMO
Project

VERIFIED

nongmoproject.org

NO DYES.

NO ARTIFICIAL FLAVORS.

NO ARTIFICIAL SWEETENERS.

SYRINGE INCLUDED

2 FL OZ (59 mL)